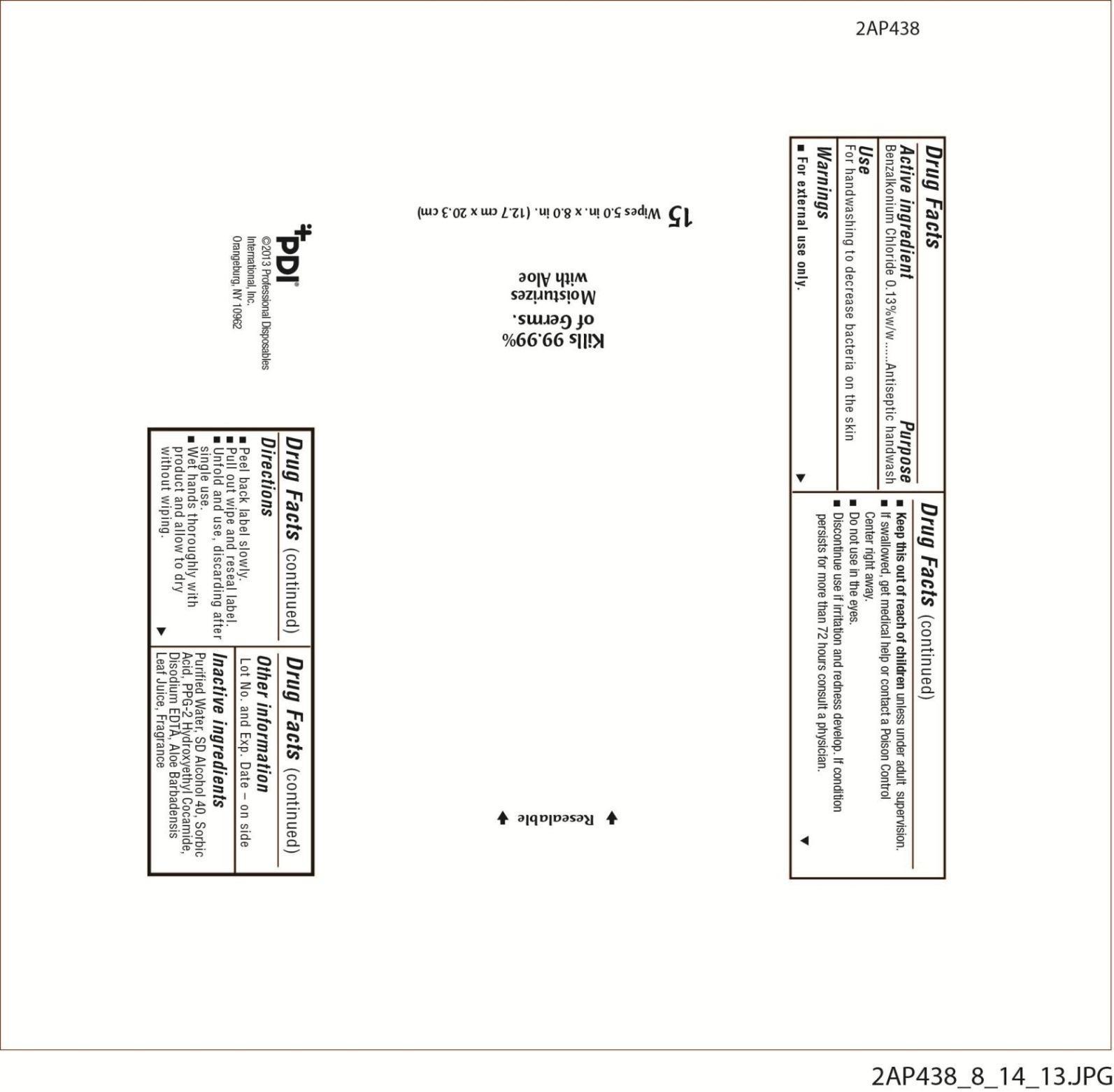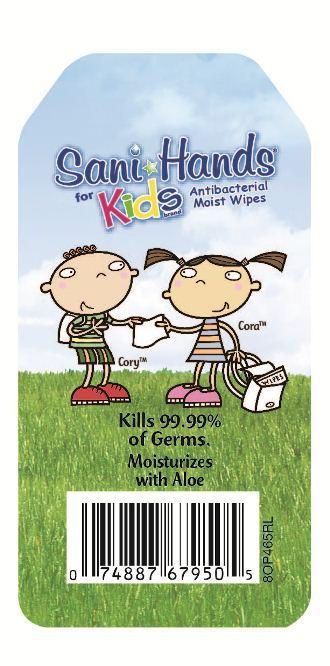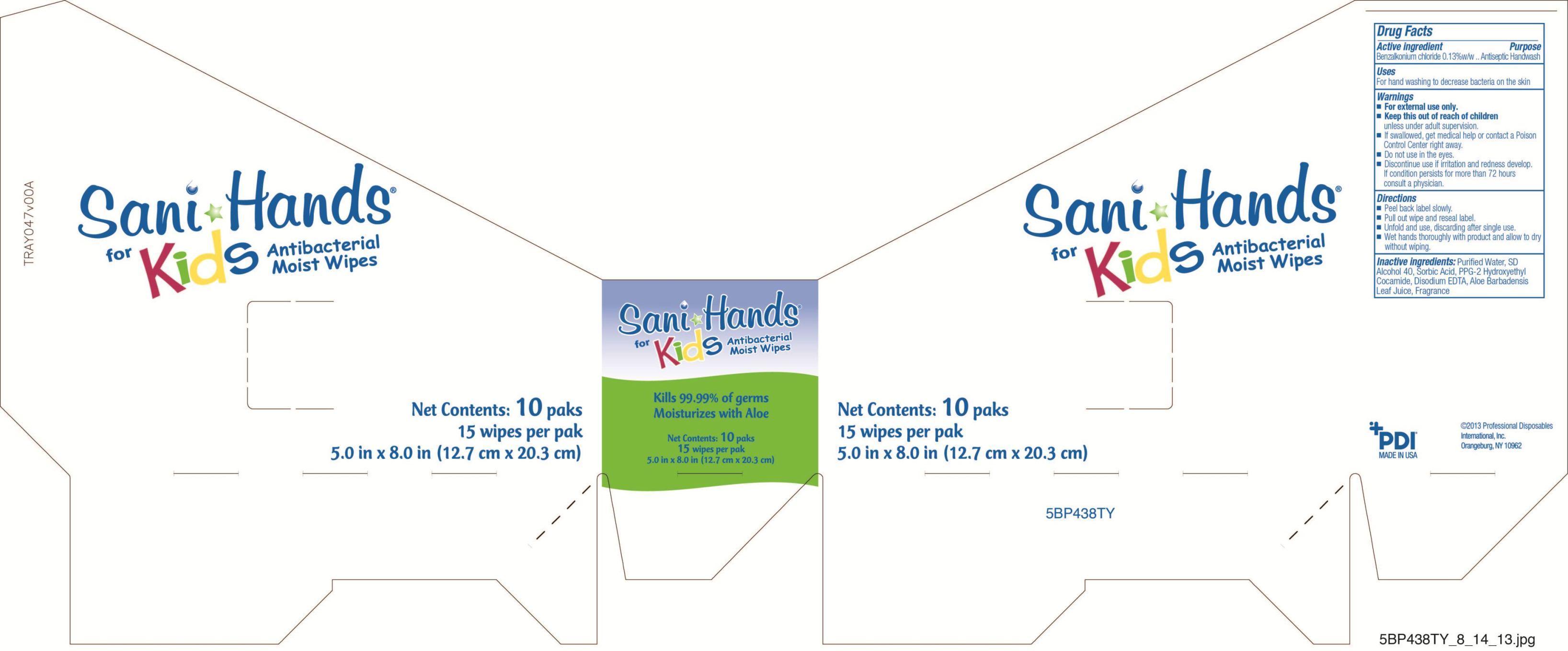 DRUG LABEL: Sani-Hands for Kids
NDC: 10819-7010 | Form: CLOTH
Manufacturer: Professional Disposables International, Inc.
Category: otc | Type: HUMAN OTC DRUG LABEL
Date: 20131226

ACTIVE INGREDIENTS: Benzalkonium Chloride 0.13 mg/1 mL
INACTIVE INGREDIENTS: WATER; ALCOHOL; SORBIC ACID; COCO DIETHANOLAMIDE; EDETATE DISODIUM; ALOE VERA LEAF; MICROCITRUS AUSTRALIS FRUIT

SANI-HANDS FOR KIDS ANTIBACTERIAL MOIST WIPES

Use

For hand washing to decrease bacteria on the skin

Warnings

- For external use only.
- If swallowed, get medical help or contact a Poison Control Center right away.
- Do not use in the eyes.
- Flammable, keep away from fire or flame.
- Discontinue use if irritation and redness develop. If condition persists for more than 72 hours consult a doctor.

Keep out of reach of children.

Directions

- Peel back label slowly.
- Pull out wipe and reseal label.
- Unfold and use; discard after single use.
- Wet hands thoroughly with product and allow to dry without wiping.

Other information

Lot No. and Exp. date - on side

Dosage

Wet hands thoroughly with product and allow to dry without wiping.

Inactive ingredients

Water, SD Alcohol 40, Sorbic Acid, PPG-2 Hydroxyethyl Cocamide, Disodium EDTA, Aloe Barbadensis Leaf Juice, Fragrance

Professional Disposables International, Inc.
Orangeburg, NY 10962-1376 - USA - 1-800-999-6423
Made in USA

Principal Display Panel - 10 Count

Sani-Hands for Kids
Antibacterial Moist Wipes
Kills 99.99% of Germs
Moisturizes with Aloe
15 wipes per Paks [5.0 in x 8.0 in (12.7 cm x 20.3 cm)] 10 Paks per Tray

Flow Wrap Label
Reseal label
Tray Label

Active ingredient

Benzalkonium Chloride 0.13% w/w

Purpose

Antiseptic handwash